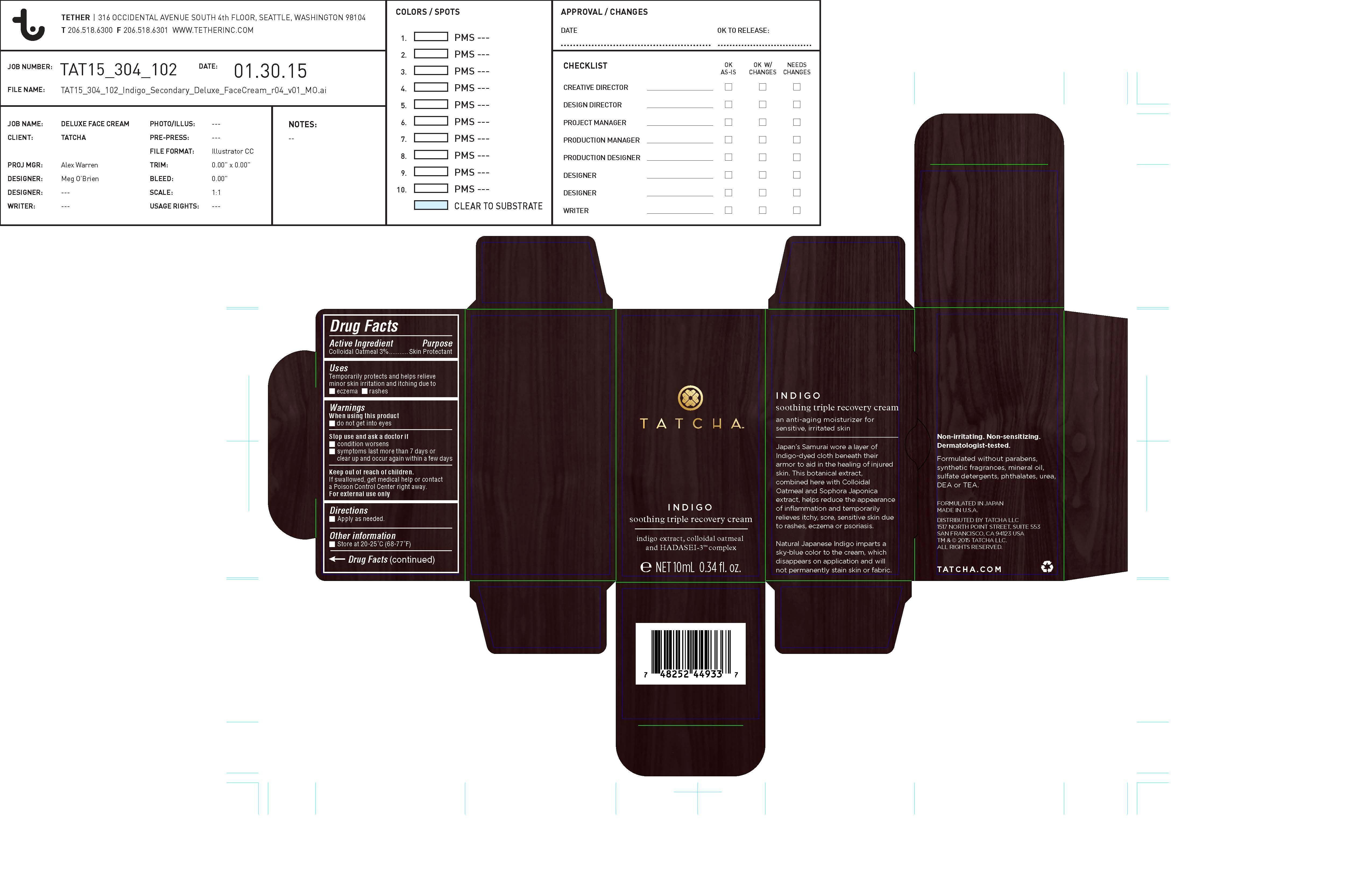 DRUG LABEL: INDIGO soothing triple recovery cream
NDC: 69417-100 | Form: LOTION
Manufacturer: TATCHA INC.
Category: otc | Type: HUMAN OTC DRUG LABEL
Date: 20150616

ACTIVE INGREDIENTS: OATMEAL 3 g/50 g
INACTIVE INGREDIENTS: WATER; SQUALANE; GLYCERIN; PROPANEDIOL; DIMETHICONE CROSSPOLYMER (450000 MPA.S AT 12% IN CYCLOPENTASILOXANE); DIISOSTEARYL MALATE; ORYZA SATIVA WHOLE; XYLITOL; BEHENETH-20; SODIUM ACRYLATE; SORBITAN TRISTEARATE; DIMETHICONE/DIENE DIMETHICONE CROSSPOLYMER; ETHYLHEXYLGLYCERIN; PHENOXYETHANOL; DIMETHICONE; TITANIUM DIOXIDE; MICA; COCOS NUCIFERA WHOLE; INOSITOL; AMORPHOPHALLUS KONJAC ROOT; DISODIUM EDTA-COPPER; INDIGOFERA TINCTORIA LEAF; SERICIN 1; ETHYLHEXYL PALMITATE; CAMELLIA SINENSIS WHOLE; CHONDRUS CRISPUS; AVENA SATIVA WHOLE; PRUNUS APETALA WHOLE; SOPHORA FLAVESCENS WHOLE; DEXTRAN 1; CALCIUM CARBONATE; POLYGONUM ARENASTRUM WHOLE

DRUG FACTS

Purpose

Skin Protectant

Active Ingredients

Colloidal Oatmeal 3.00%

Uses

Temporarily protects and helps releive minor skin irritation and itching due to eczema rashes

Warnings

When using this product do not get into eyes

Stop use and ask a doctor if

- condition worsens
- symptoms last more than 7 days or clear up and occur again within a few days

Keep out of reach of children. If swalled, get medical help or contact a Poison Control Center right away.

Directions

- Apply as needed.

Inactive Ingredients

WATER, SQUALANE, GLYCERIN, PROPANEDIOL, CYCLOPENTASILOXANE,
DIISOSTEARYL MALATE, ORYZA SATIVA (RICE) BRAN WAX, XYLITOL,
BEHENYL ALCOHOL, POLYGONUM TINCTORIUM (JAPANESE INDIGO)
LEAF/STEM EXTRACT, INDIGOFERA TINCTORIA LEAF EXTRACT, AVENA
SATIVA (OAT) KERNEL EXTRACT, CAMELLIA SINENSIS (GREEN TEA) LEAF
EXTRACT, COCOS NUCIFERA (COCONUT) OIL, SOPHORA JAPONICA FLOWER
EXTRACT, PRUNUS LANNESIANA FLOWER EXTRACT, ORYZA SATIVA (RICE)
GERM OIL, INOSITOL (RICE EXTRACT), SERICIN (SILK EXTRACT),
TETRASODIUM TETRACARBOXYMETHYL NARINGENINCHALCONE,
CHONDRUS CRISPUS (RED ALGAE) EXTRACT, AMORPHOPHALLUS KONJAC
ROOT POWDER, SODIUM HYALURONATE, DEXTRIN, SORBITAN
TRISTEARATE, TRIHYDROXYSTEARIN, DIMETHICONE, DIMETHICONE/VINYL
DIMETHICONE CROSSPOLYMER, BEHENETH-20, BIS-DIGLYCERYL
POLYACYLADIPATE-2, ETHYLHEXYLGLYCERIN, SODIUM
DILAURAMIDOGLUTAMIDE LYSINE, DISODIUM EDTA, ETHYLHEXYL
PALMITATE, SODIUM ACRYLATE/ACRYLOYLDIMETHYLTAURATE/
DIMETHYLACRYLAMIDE CROSSPOLYMER, TITANIUM DIOXIDE, CALCIUM
CARBONATE, TIN OXIDE, PHENOXYETHANOL, MICA

Other Information

Store at 20-25C (68-77)F